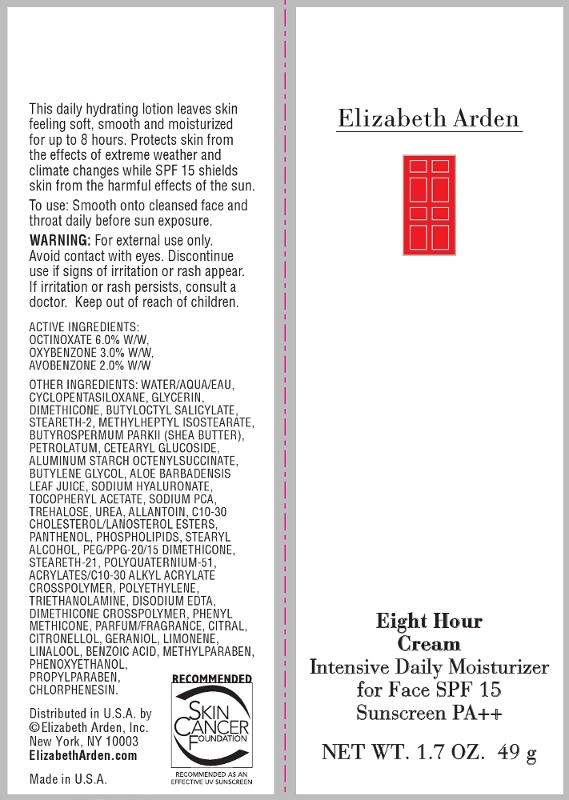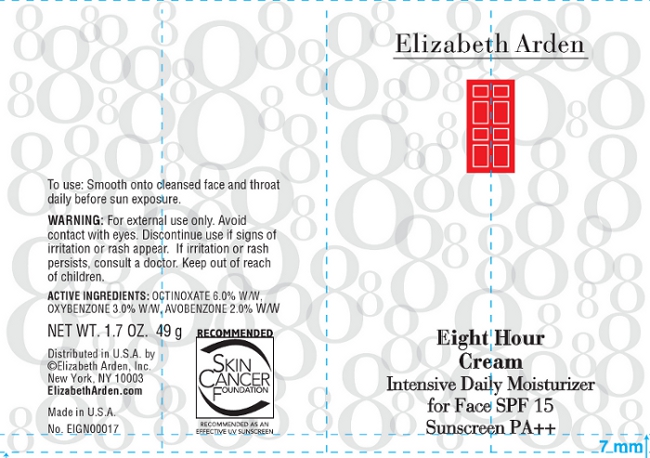 DRUG LABEL: Eight Hour Cream Intensive Daily Moisturizer For Face SPF 15
NDC: 67938-0866 | Form: CREAM
Manufacturer: Elizabeth Arden, Inc
Category: otc | Type: HUMAN OTC DRUG LABEL
Date: 20110727

ACTIVE INGREDIENTS: OCTINOXATE 2.94 g/49 g; OXYBENZONE 1.47 g/49 g; AVOBENZONE 0.98 g/49 g
INACTIVE INGREDIENTS: WATER; GLYCERIN; DIMETHICONE; BUTYLOCTYL SALICYLATE; STEARETH-2; SHEA BUTTER; PETROLATUM; CETEARYL GLUCOSIDE; ALUMINUM STARCH OCTENYLSUCCINATE; BUTYLENE GLYCOL; HYALURONATE SODIUM; TREHALOSE; UREA; ALLANTOIN; C10-30 CHOLESTEROL/LANOSTEROL ESTERS; PANTHENOL; STEARYL ALCOHOL; STEARETH-21; CITRAL; GERANIOL; BENZOIC ACID; METHYLPARABEN; PHENOXYETHANOL; PROPYLPARABEN; CHLORPHENESIN

BB0866

DESCRIPTION

This daily hydrating lotion leaves skin feeling soft, smooth, and moisturized for up to 8 hours. Protects skin from the effects of extreme weather and climate changes while SPF 15 shields from the harmful effects of the sun.

INDICATIONS AND USAGE

To Use: Smooth on to cleansed face and throat daily before sun exposure.

WARNINGS

Warning: For external use only. Avoid contact with eyes. Discontinue use if signs of irritation or rash appear. If irritation or rash persists, consult a doctor. Keep out of reach of children.

OTC - ACTIVE INGREDIENT

Active Ingredients: Octinoxate 6.0% W/W, Oxybenzone 3.0% W/W, Avobenzone 2.0% W/W.

INACTIVE INGREDIENT

Other Ingredients: Water/Aqua/Eau, Cyclopentasiloxane, Glycerin, Dimethicone, Butyloctyl Salicylate, Steareth-2, Methylheptyl Isostearate, Butyrospermum Parkii (Shea Butter), Petrolatum, Cetearyl Glucoside, Aluminum Starch Octenylsuccinate, Butylene Glycol, Aloe Barbadensis Leaf Juice, Sodium Hyaluronate, Tocopheryl Acetate, Sodium PCA, Trehalose, Urea, Allantoin, C10-30 Cholesterol/Lanosterol Esters, Panthenonl, Phospholipids, Stearyl Alcohol, PEG/PPG-20/15 Dimethicone, Seareth-21, Polyquaternium-51, Acrylates/C10-30 Alkyl Acrylate Crosspolymer, Polethylene, Triethanolamine, Disodium EDTA, Dimethicone Crosspolymer Phenyl Methicone, Parfum/Fragrance, Citral, Citronellol, Geraniol, Limonene, Linalool, Benzoic Acid, Methyparaben, Phenoxyethanol, Chlorphenesin.

DOSAGE & ADMINISTRATION

Smooth on to face.

OTC - KEEP OUT OF REACH OF CHILDREN

Keep out of reach of children.

OTC - PURPOSE

Provides SPF 15 sun protection.

OTC - WHEN USING

Avoid contact with eyes.